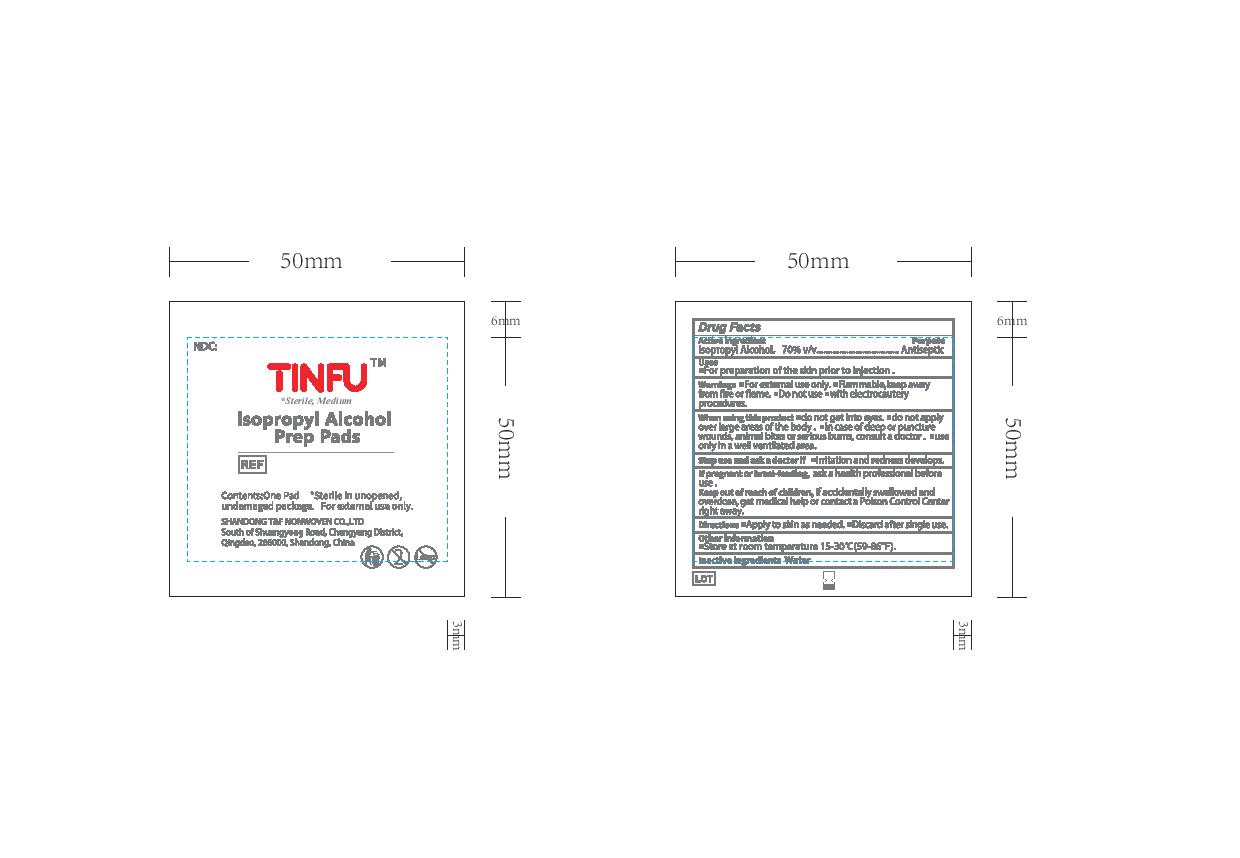 DRUG LABEL: Tinfu Isopropyl Alcohol Prep Pads
NDC: 82167-000 | Form: CLOTH
Manufacturer: Shandong T&F Medical Technology Co., Ltd
Category: otc | Type: HUMAN OTC DRUG LABEL
Date: 20231115

ACTIVE INGREDIENTS: ISOPROPYL ALCOHOL 0.7 mL/1 mL
INACTIVE INGREDIENTS: WATER

This is a hand sanitizer manufactured according to the Temporary Policy for Preparation of Certain Alcohol-Based Hand Sanitizer Products During the Public Health Emergency (CoViD-19); Guidance for Industry.

The hand sanitizer is manufactured using only the following United States Pharmacopoeia (USP) grade ingredients in the preparation of the product (percentage in final product formulation) consistent with World Health Organization (WHO) recommendations:

1. Isopropyl Alcohol (75%, v/v) in an aqueous solution denatured according to Alcohol and Tobacco Tax and Trade Bureau regulations in 27 CFR part 20.
2. Glycerol (1.45% v/v).
3. Hydrogen peroxide (0.125% v/v).
4. Sterile distilled water or boiled cold water.

The firm does not add other active or inactive ingredients. Different or additional ingredients may impact the quality and potency of the product.

Active Ingredient(s)

Isopropyl Alcohol, 70% v/v

Purpose

Antiseptic

Use

For preparation of the skin prior to injection.

Warnings

For external use only. Flammable,keep away from fire or flame.

Do not use

- with electrocautery procedures.

When using this product do not get into eyes. do not apply over large areas of the body. in case of deep or puncture wounds, animal bites or serious burns, consult a doctor. use only in a well ventilated area.

Stop use and ask a doctor if irritation and redness develops.

FEMALES AND MALES OF REPRODUCTIVE POTENTIAL

If pregnant or breastfeeding ask a health professional before use.

Keep out of reach of children. If accidentally swallowed, get medical help or contact a Poison Control Center right away.

Directions

- Apply to skin as needed.
- Discard after single use.

Other information

- Store at room temperature 15-30C (59-86F)

Inactive ingredients

Water

Package Label - Principal Display Panel

NDC: 82167-000